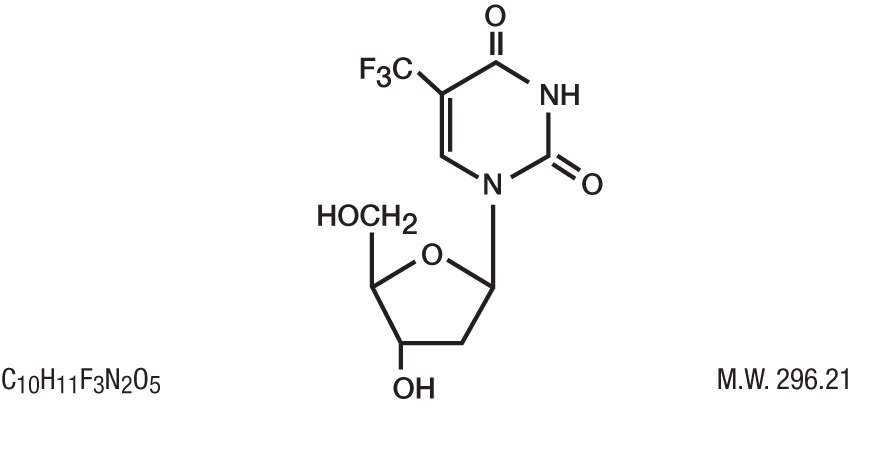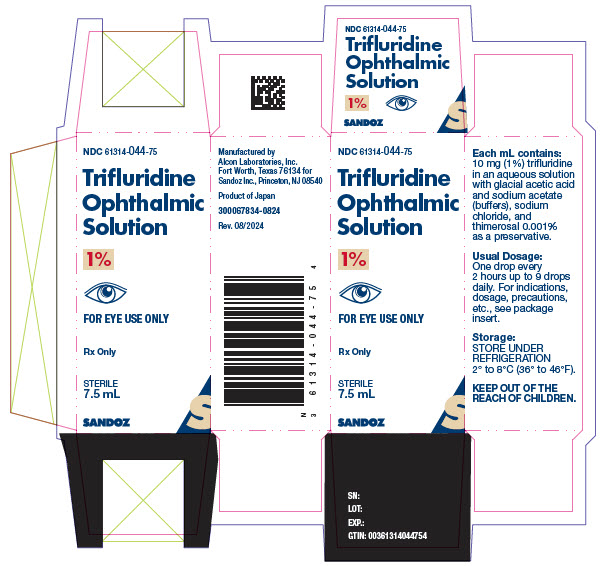 DRUG LABEL: Trifluridine
NDC: 61314-044 | Form: SOLUTION
Manufacturer: Sandoz Inc
Category: prescription | Type: HUMAN PRESCRIPTION DRUG LABEL
Date: 20240801

ACTIVE INGREDIENTS: TRIFLURIDINE 10 mg/1 mL
INACTIVE INGREDIENTS: ACETIC ACID; SODIUM ACETATE; SODIUM CHLORIDE; THIMEROSAL

TRIFLURIDINE OPHTHALMIC SOLUTION, 1%

DESCRIPTION

DESCRIPTION: Trifluridine Ophthalmic Solution (also known as trifluorothymidine, F3TdR, F3T), an antiviral drug for topical treatment of epithelial keratitis caused by herpes simplex virus. The chemical name of trifluridine is α,α,α-trifluorothymidine. Trifluridine has the following structural formula.

Trifluridine sterile ophthalmic solution contains 1% trifluridine in an aqueous solution with acetic acid and sodium acetate (buffers), sodium chloride, and thimerosal 0.001% (added as a preservative). The pH range is 5.5 to 6.0 and osmolality is approximately 283 mOsm.

CLINICAL PHARMACOLOGY

CLINICAL PHARMACOLOGY: Trifluridine is a fluorinated pyrimidine nucleoside with in vitro and in vivo activity against herpes simplex virus, types 1 and 2 and vacciniavirus. Some strains of adenovirus are also inhibited in vitro.

Trifluridine is also effective in the treatment of epithelial keratitis that has not responded clinically to the topical administration of idoxuridine or when ocular toxicity or hypersensitivity to idoxuridine has occurred. In a smaller number of patients found to be resistant to topical vidarabine, trifluridine was also effective.

Trifluridine interferes with DNA synthesis in cultured mammalian cells. However, its antiviral mechanism of action is not completely known.

In vitro perfusion studies on excised rabbit corneas have shown that trifluridine penetrates the intact cornea as evidenced by recovery of parental drug and its major metabolite, 5-carboxy-2´-deoxyuridine, on the endothelial side of the cornea. Absence of the corneal epithelium enhances the penetration of trifluridine approximately two-fold.

Intraocular penetration of trifluridine occurs after topical instillation of trifluridine into human eyes. Decreased corneal integrity or stromal or uveal inflammation may enhance the penetration of trifluridine into the aqueous humor. Unlike the results of ocular penetration of trifluridine in vitro, 5-carboxy-2´-deoxyuridine was not found in detectable concentrations within the aqueous humor of the human eye.

Systemic absorption of trifluridine following therapeutic dosing with trifluridine appears to be negligible. No detectable concentrations of trifluridine or 5-carboxy-2´-deoxyuridine were found in the sera of adult healthy normal subjects who had trifluridine instilled into their eyes seven times daily for 14 consecutive days.

Clinical Studies: During a controlled multicenter clinical trial, 92 of 97 (95%) patients (78 of 81 with dendritic and 14 of 16 with geographic ulcers) responded to therapy with trifluridine as evidenced by complete corneal re-epithelialization within the 14-day therapy period. Fifty-six of 75 (75%) patients (49 of 58 with dendritic and 7 of 17 with geographic ulcers) responded to idoxuridine therapy. The mean time to corneal re-epithelialization for dendritic ulcers (6 days) and geographic ulcers (7 days) was similar for both therapies.

In other clinical studies, trifluridine was evaluated in the treatment of herpes simplex virus keratitis in patients who were unresponsive or intolerant to the topical administration of idoxuridine or vidarabine. Trifluridine was effective in 138 of 150 (92%) patients (109 of 114 with dendritic and 29 of 36 with geographic ulcers) as evidenced by corneal re-epithelialization. The mean time to corneal re-epithelialization was 6 days for patients with dendritic ulcers and 12 days for patients with geographic ulcers.

The clinical efficacy of trifluridine in the treatment of stromal keratitis and uveitis due to herpes simplex virus or ophthalmic infections caused by vacciniavirus and adenovirus has not been established by well-controlled clinical trials. Trifluridine has not been shown to be effective in the prophylaxis of herpes simplex virus keratoconjunctivitis and epithelial keratitis by well-controlled clinical trials. Trifluridine is not effective against bacterial, fungal or chlamydial infections of the cornea or nonviral trophic lesions.

INDICATIONS AND USAGE: Trifluridine Ophthalmic Solution is indicated for the treatment of primary keratoconjunctivitis and recurrent epithelial keratitis due to herpes simplex virus, types 1 and 2.

CONTRAINDICATIONS

CONTRAINDICATIONS: Trifluridine Ophthalmic Solution is contraindicated for patients who develop hypersensitivity reactions or chemical intolerance to trifluridine.

WARNINGS

WARNINGS: The recommended dosage and frequency of administration should not be exceeded (See DOSAGE AND ADMINISTRATION).

PRECAUTIONS

PRECAUTIONS: General: Trifluridine Ophthalmic Solution should be prescribed only for patients who have a clinical diagnosis of herpetic keratitis.

Trifluridine may cause mild local irritation of the conjunctiva and cornea when instilled but these effects are usually transient.

Although documented in vitro viral resistance to trifluridine has not been reported following multiple exposure to trifluridine, the possibility of the development of viral resistance exists.

CARCINOGENESIS AND MUTAGENESIS AND IMPAIRMENT OF FERTILITY

Carcinogenesis, Mutagenesis, Impairment of Fertility: Mutagenic Potential: Trifluridine has been shown to exert mutagenic, DNA-damaging and cell-transforming activities in various standard in vitro test systems, and clastogenic activity in Vicia faba cells. It did not induce chromosome aberrations in bone marrow cells of male or female rats following a single subcutaneous dose of 100 mg/kg, but was weakly positive in female, but not in male, rats following daily subcutaneous administration at 700mg/kg/day for 5 days.

Although the significance of these test results is not clear or fully understood, there exists the possibility that mutagenic agents may cause genetic damage in humans.

Oncogenic Potential: Lifetime carcinogenicity bioassays in rats and mice given daily subcutaneous doses of trifluridine have been performed. Rats tested at 1.5, 7.5, and 15 mg/kg/day had increased incidences of adenocarcinomas of the intestinal tract and mammary glands, hemangiosarcomas of the spleen and liver, carcinosarcomas of the prostate gland and granulosathecal cell tumors of the ovary. Mice were tested at 1, 5 and 10 mg/kg/day; those given 10mg/kg/day trifluridine had significantly increased incidences of adenocarcinomas of the intestinal tract and uterus. Those given 10 mg/kg/day also had a significantly increased incidence of testicular atrophy as compared to vehicle control mice.

PREGNANCY

Pregnancy: Teratogenic Effects: Trifluridine was not teratogenic at doses up to 5 mg/kg/day (23 times the estimated human exposure) when given subcutaneously to rats and rabbits. However, fetal toxicity consisting of delayed ossification of portions of the skeleton occurred at dose levels of 2.5 and 5 mg /kg /day in rats and at 2.5 mg/kg/day in rabbits. In addition, both 2.5 and 5 mg/kg/day produced fetal death and resorption in rabbits. In both rats and rabbits, 1 mg/kg/day (5 times the estimated human exposure) was a no-effect level. There were no teratogenic or fetotoxic effects after topical application of trifluridine (approximately 5 times the estimated human exposure) to the eyes of rabbits on the 6th through the 18th days of pregnancy. In a non-standard test, trifluridine solution has been shown to be teratogenic when injected directly into the yolk sac of chicken eggs. There are no adequate and well-controlled studies in pregnant women. Trifluridine Ophthalmic Solution should be used during pregnancy only if the potential benefit justifies the potential risk to the fetus.

NURSING MOTHERS

Nursing Mothers: It is unlikely that trifluridine is excreted in human milk after ophthalmic instillation of trifluridine because of the relatively small dosage (5mg/day), its dilution in body fluids and its extremely short half-life (approximately 12 minutes). The drug should not be prescribed for nursing mothers unless the potential benefits outweigh the potential risks.

PEDIATRIC USE

Pediatric Use: Safety and effectiveness in pediatric patients below six years of age have not been established.

GERIATRIC USE

Geriatric Use: No overall differences in safety or effectiveness have been observed between elderly and younger patients.

ADVERSE REACTIONS

ADVERSE REACTIONS: The most frequent adverse reactions reported during controlled clinical trials were mild, transient burning or stinging upon instillation (4.6%) and palpebral edema (2.8%). Other adverse reactions in decreasing order of reported frequency were superficial punctate keratopathy, epithelial keratopathy, hypersensitivity reaction, stromal edema, irritation, keratitis sicca, hyperemia, and increased intraocular pressure.

OVERDOSAGE

OVERDOSAGE: Overdosage by ocular instillation is unlikely because any excess solution should be quickly expelled from the conjunctival sac.

Acute overdosage by accidental oral ingestion of trifluridine has not occurred. However, should such ingestion occur, the 75 mg dosage of trifluridine in a 7.5 mL bottle of Trifluridine Ophthalmic Solution is not likely to produce adverse effects. Single intravenous doses of 1.5 to 30 mg/kg/day in children and adults with neoplastic disease produce reversible bone marrow depression as the only potentially serious toxic effect and only after three to five courses of therapy. The acute oral LD50 in the mouse and rat was 4379 mg/kg or higher.

DOSAGE AND ADMINISTRATION: Instill one drop of Trifluridine Ophthalmic Solution onto the cornea of the affected eye every 2 hours while awake for a maximum daily dosage of nine drops until the cornea ulcer has completely re-epithelialized. Following re-epithelialization, treatment for an additional 7 days of one drop every 4 hours while awake for a minimum daily dosage of five drops is recommended.

If there are no signs of improvement after 7 days of therapy or complete re-epithelialization has not occurred after 14 days of therapy, other forms of therapy should be considered. Continuous administration of trifluridine for periods exceeding 21 days should be avoided because of potential ocular toxicity.

HOW SUPPLIED

HOW SUPPLIED: Trifluridine Ophthalmic Solution, 1% in a 7.5 mL fill packaged in a natural plastic bottle with a natural plastic flat tip and a white plastic closure.

7.5mL-NDC 61314-044-75

Store under refrigeration 2-8°C (36-46°F).

ANIMAL PHARMACOLOGY AND OR TOXICOLOGY

ANIMAL PHARMACOLOGY AND ANIMAL TOXICOLOGY: Corneal wound healing studies in rabbits showed that trifluridine did not significantly retard closure of epithelial wounds. However, mild toxic changes such as intracellular edema of the basal cell layer, mild thinning of the overlying epithelium and reduced strength of stromal wounds were observed.

Whereas instillation of trifluridine into rabbit eyes during a subchronic toxicity study produced some degree of corneal epithelial thinning, a 12-month chronic toxicity study in rabbits in which trifluridine was instilled into eyes in intermittent, multiple, full-therapy courses showed no drug-related changes in the cornea.

Rx Only

Manufactured by

Alcon Laboratories, Inc.

Fort Worth, Texas 76134 for

Sandoz Inc.

Princeton, NJ 08540

Rev. August 2024

300067836-0824

PRINCIPAL DISPLAY PANEL

NDC 61314-044-75

Trifluridine

Ophthalmic

Solution

1%

FOR EYE USE ONLY

Rx Only

STERILE

7.5 mL

SANDOZ